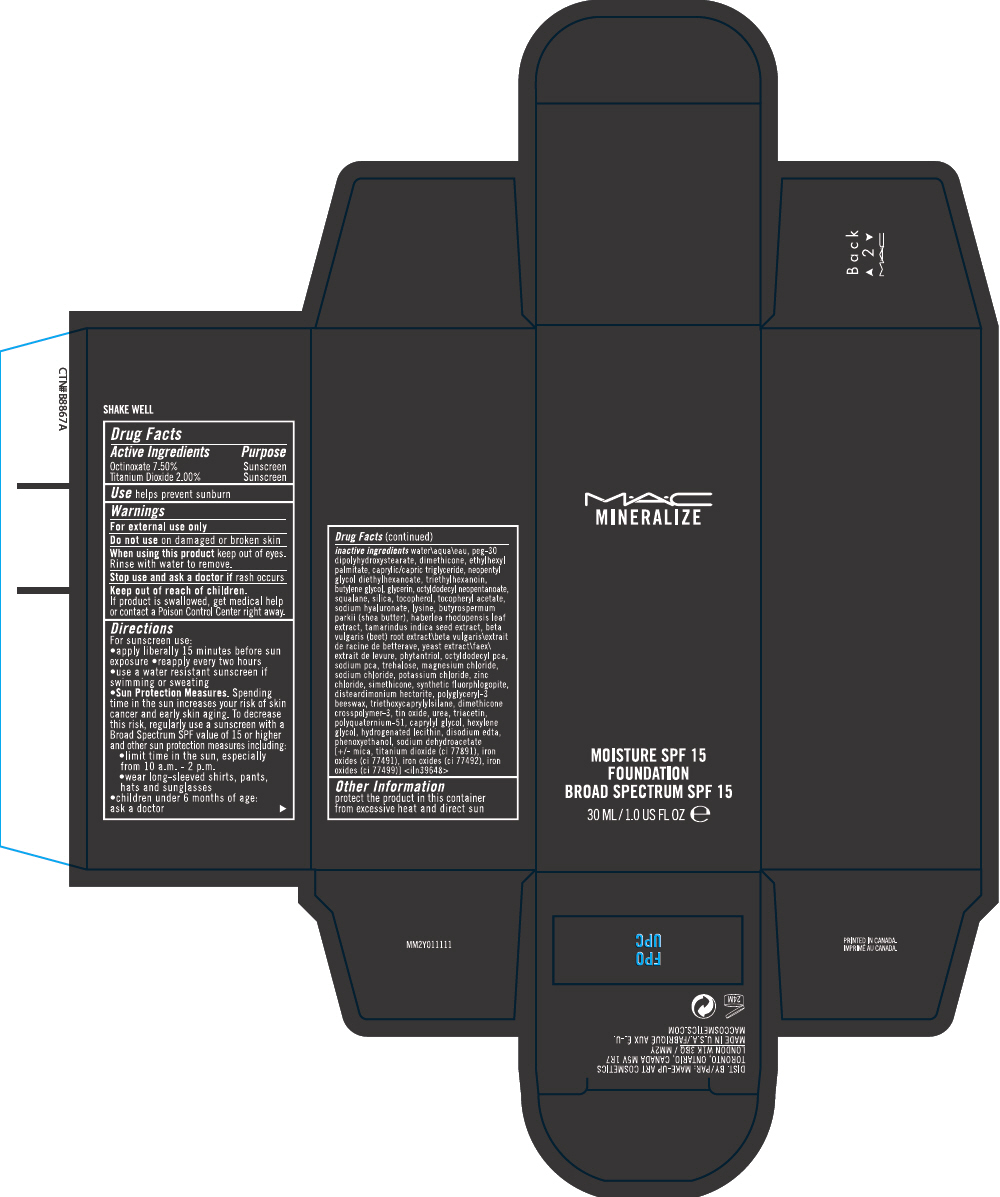 DRUG LABEL: MINERALIZE 
NDC: 40046-0061 | Form: LIQUID
Manufacturer: MAKEUP ART COSMETICS
Category: otc | Type: HUMAN OTC DRUG LABEL
Date: 20120723

ACTIVE INGREDIENTS: OCTINOXATE 7.5 mL/100 mL; TITANIUM DIOXIDE 2 mL/100 mL
INACTIVE INGREDIENTS: water; peg-30 dipolyhydroxystearate; dimethicone; ethylhexyl palmitate; medium-chain triglycerides; neopentyl glycol diethylhexanoate; triethylhexanoin; butylene glycol; glycerin; octyldodecyl neopentanoate; squalane; silicon dioxide; tocopherol; .alpha.-tocopherol acetate; hyaluronate sodium; lysine; shea butter; haberlea rhodopensis leaf; tamarind seed; beta vulgaris; yeast; phytantriol; sodium pyrrolidone carboxylate; trehalose; magnesium chloride; sodium chloride; potassium chloride; zinc chloride; triethoxycaprylylsilane; stannic oxide; urea; triacetin; caprylyl glycol; hexylene glycol; edetate disodium; phenoxyethanol; sodium dehydroacetate; mica; ferric oxide red; ferric oxide yellow; ferrosoferric oxide

MINERALIZE MOISTURE SPF 15 FOUNDATION

Drug Facts

ACTIVE INGREDIENT

Active Ingredients | Purpose
Octinoxate 7.50% | Sunscreen
Titanium Dioxide 2.00% | Sunscreen

Use

helps prevent sunburn

Warnings

For external use only

Do not use on damaged or broken skin

When using this product keep out of eyes. Rinse with water to remove.

Stop use and ask a doctor if rash occurs

Keep out of reach of children. If product is swallowed, get medical help or contact a Poison Control Center right away.

Directions

For sunscreen use:

- apply liberally 15 minutes before sun exposure
- reapply every two hours
- use a water resistant sunscreen if swimming or sweating
- Sun Protection Measures. Spending time in the sun increases your risk of skin cancer and early skin aging. To decrease this risk, regularly use a sunscreen with a Broad Spectrum SPF value of 15 or higher and other sun protection measures including:
  - limit time in the sun, especially from 10 a.m. - 2 p.m.
  - wear long-sleeved shirts, pants, hats and sunglasses
- children under 6 months of age: ask a doctor

inactive ingredients

water\aqua\eau, peg-30 dipolyhydroxystearate, dimethicone, ethylhexyl palmitate, caprylic/capric triglyceride, neopentyl glycol diethylhexanoate, triethylhexanoin, butylene glycol, glycerin, octyldodecyl neopentanoate, squalane, silica, tocopherol, tocopheryl acetate, sodium hyaluronate, lysine, butyrospermum parkii (shea butter), haberlea rhodopensis leaf extract, tamarindus indica seed extract, beta vulgaris (beet) root extract\beta vulgaris\extrait de racine de betterave, yeast extract\faex\extrait de levure, phytantriol, octyldodecyl pca, sodium pca, trehalose, magnesium chloride, sodium chloride, potassium chloride, zinc chloride, simethicone, synthetic fluorphlogopite, disteardimonium hectorite, polyglyceryl-3 beeswax, triethoxycaprylylsilane, dimethicone crosspolymer-3, tin oxide, urea, triacetin, polyquaternium-51, caprylyl glycol, hexylene glycol, hydrogenated lecithin, disodium edta, phenoxyethanol, sodium dehydroacetate [+/- mica, titanium dioxide (ci 77891), iron oxides (ci 77491), iron oxides (ci 77492), iron oxides (ci 77499)] <iln 39648>

Other Information

protect the product in this container from excessive heat and direct sun

DIST. BY/PAR: MAKE-UP ART COSMETICS
TORONTO, ONTARIO, CANADA M5V 1R7
LONDON W1K 3BQ / MM2Y

PRINCIPAL DISPLAY PANEL - 30 ML Bottle Carton

M•A•C
MINERALIZE

MOISTURE SPF 15
FOUNDATION
BROAD SPECTRUM SPF 15

30 ML/1.0 US FL OZ e